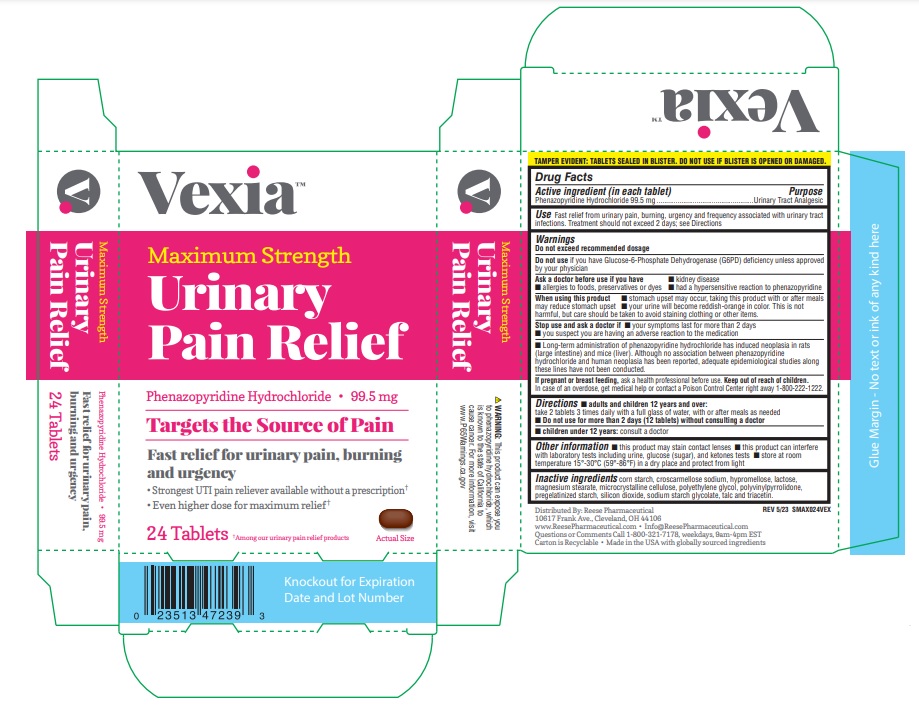 DRUG LABEL: Vexia Maximum Strength Urinary Pain Relief
NDC: 10956-703 | Form: TABLET
Manufacturer: Reese Pharmaceutical Co
Category: otc | Type: HUMAN OTC DRUG LABEL
Date: 20251229

ACTIVE INGREDIENTS: PHENAZOPYRIDINE HYDROCHLORIDE 99.5 mg/1 1
INACTIVE INGREDIENTS: LACTOSE; MAGNESIUM SILICATE

DRUG FACTS

Active ingredient (in each tablet)

Phenazopyridine Hydrochloride 99.5 mg .

Purpose

Urinary Analgesic

Warnings

Do not exceed recommended dosage

Ask doctor before use if you have

■ kidney disease
■ allergies to food, preservatives or dyes
■ had a hypersensitive reaction to phenazopyridine

When using this product

■ stomach upset may occur, taking this product with or after meals may
reduce stomach upset
■ your urine will become reddish-orange in color. This is not harmful, but
care should be taken to avoid staining clothing or other items.

Stop use and ask doctor if

■ your symptoms last for more than 2 days
■ you suspect you are having an adverse reaction to the medication

If pregnant or breast feeding,

Ask a health professional before use.

Keep out of reach of children

In case of an overdose, get medical help or contact a Poison Control Center right away.

Use

Fast relief from urinary pain, burning, urgency and frequency associated with urinary tract
infections.

Inactive ingredients

Lactose, magnesium silicate, magnesium stearate, microcrystalline cellulose, pharmaceutical glaze, and sodium starch glycolate.

Directions

■ adults and children 12 years and over:
take 2 tablets 3 times daily with a full glass of water, with or after meals as needed

■ children under 12 years: consult a doctor

■ Do not use for more than 2 days (12 tablets) without consulting a doctor